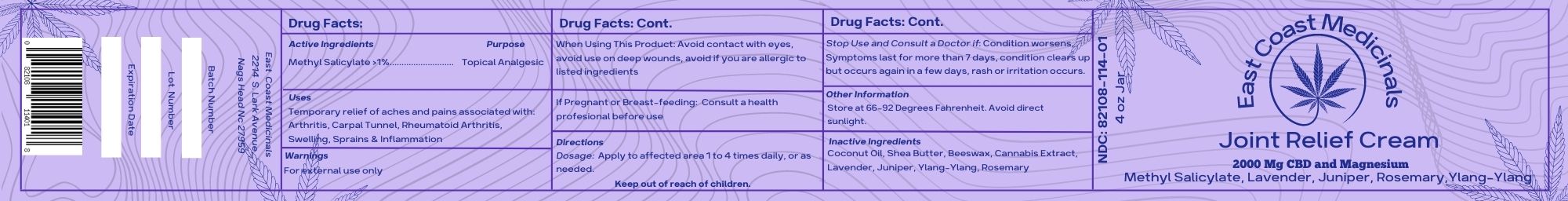 DRUG LABEL: East Coast Joint Relief
NDC: 82108-114 | Form: SALVE
Manufacturer: East Coast Medicinals
Category: homeopathic | Type: HUMAN OTC DRUG LABEL
Date: 20221209

ACTIVE INGREDIENTS: METHYL SALICYLATE 1 g/113.398 g
INACTIVE INGREDIENTS: PEG-8 BEESWAX 9 g/113.398 g; SHEA BUTTER 13.4 g/113.398 g; ROSEMARY OIL 2 g/113.398 g; JUNIPER BERRY OIL 3 g/113.398 g; CANNABIDIOL 4 g/113.398 g; YLANG-YLANG OIL 2 g/113.398 g; LAVENDER OIL 3 g/113.398 g; COCONUT OIL 75.998 g/113.398 g

East Coast Joint Relief

Active Ingredients

Methyl Salicylate >1%........................... Topical Analgesic

PURPOSE

Methyl Salicylate >1%........................... Topical Analgesic

Uses

Temporary relief of aches and pains associated with: Arthritis, Carpal Tunnel, Rheumatoid Arthritis, Swelling, Sprains & Inflammation

WARNINGS

For external use only

When Using This Product: Avoid contact with eyes, avoid use on deep wounds, avoid if you are allergic to listed ingredients

Stop Use and Consult a Doctor if: Condition worsens, Symptoms last for more than 7 days, condition clears up but occurs again in a few days, rash or irritation occurs.

PREGNANCY OR BREAST FEEDING

Dosage: Apply to affected area 1 to 4 times daily, or as needed.

DOSAGE AND ADMINISTRATION

Keep Out of Reach of Children

OTHER SAFETY INFORMATION

Store at 66-92 Degrees Fahrenheit. Avoid direct sunlight.

INACTIVE INGREDIENT

Coconut Oil, Shea Butter, Beeswax, Cannabis Extract, Lavender, Juniper, Ylang-Ylang, Rosemary